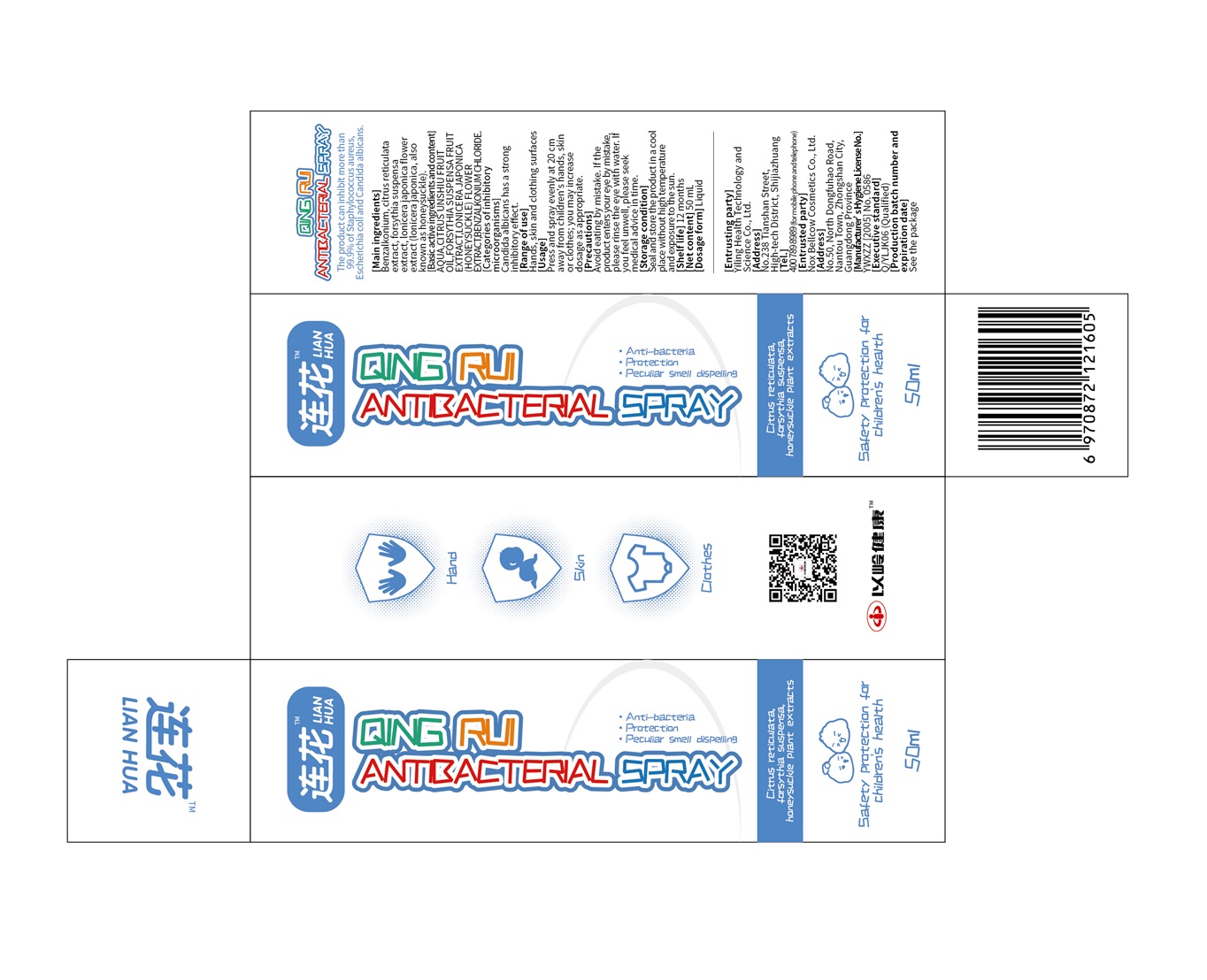 DRUG LABEL: Qingrui Antibacterial
NDC: 80945-102 | Form: LIQUID
Manufacturer: Yiling Health Science & Technology Co. Ltd.
Category: otc | Type: HUMAN OTC DRUG LABEL
Date: 20201210

ACTIVE INGREDIENTS: BENZALKONIUM CHLORIDE 0.5 mg/1 mL
INACTIVE INGREDIENTS: CITRUS RETICULATA FRUIT OIL; FORSYTHIA SUSPENSA FRUIT; LONICERA JAPONICA FLOWER; WATER

Qingrui Antibacterial

Qingrui Antibacterial

Active Ingredient(s)

Benzalkonium chloride 0.5mg/mL. Purpose: Antiseptic

Purpose

Antiseptic, Qingrui Antibacterial

Use

Qingrui Antibacterial to help reduce bacteria that potentially can cause disease. For use when soap and water are not available.

Warnings

For external use only.

Do not use

- in children less than 2 months of age
- on open skin wounds

When using this product keep out of eyes, ears, and mouth. In case of contact with eyes, rinse eyes thoroughly with water.
Stop use and ask a doctor if irritation or rash occurs. These may be signs of a serious condition.
Keep out of reach of children. If swallowed, get medical help or contact a Poison Control Center right away.

Stop use and ask a doctor if irritation or rash occurs. These may be signs of a serious condition.

Keep out of reach of children. If swallowed, get medical help or contact a Poison Control Center right away.

Directions

- Press and spray evenly at 20cm way from hangds, skin or clothes; you may increase dosage as appropriate.
- Supervise children under 6 years of age when using this product to avoid swallowing.

Other information

- Store between 15-30C (59-86F)
- Avoid freezing and excessive heat above 40C (104F)

Inactive ingredients

AQUA
CITRUS UNSHIU FRUIT OIL
FORSYTHIA SUSPENSA FRUIT EXTRACT
LONICERA JAPONICA (HONEYSUCKLE) FLOWER EXTRACT